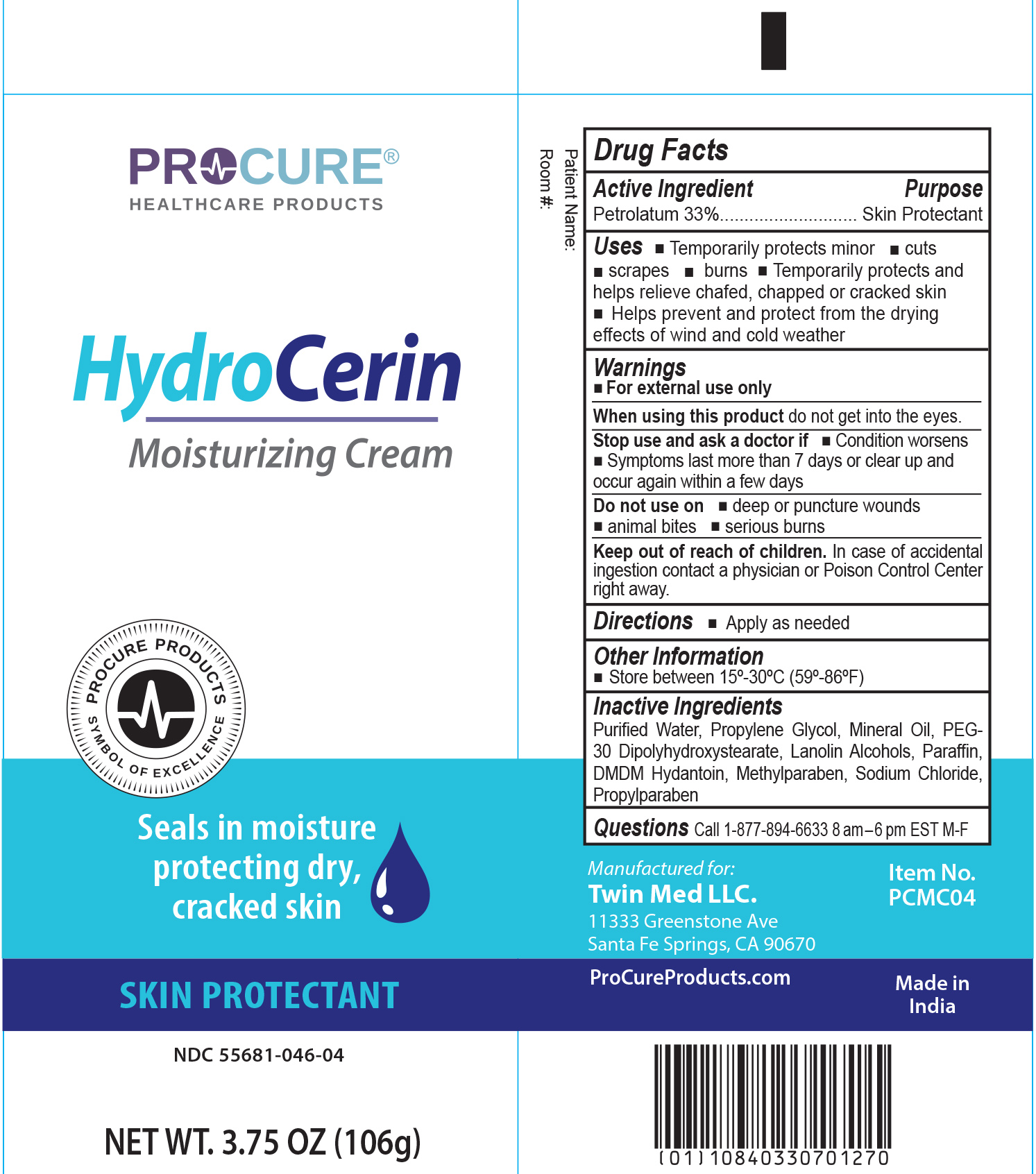 DRUG LABEL: ProCure HydroCerin
NDC: 55681-046 | Form: CREAM
Manufacturer: Twin Med LLC
Category: otc | Type: HUMAN OTC DRUG LABEL
Date: 20250825

ACTIVE INGREDIENTS: PETROLATUM 33 g/100 g
INACTIVE INGREDIENTS: PEG-30 DIPOLYHYDROXYSTEARATE (4000 MW); LANOLIN ALCOHOLS; WATER; PROPYLPARABEN; SODIUM CHLORIDE; DMDM HYDANTOIN; PARAFFIN; MINERAL OIL; PROPYLENE GLYCOL; METHYLPARABEN

Active Ingredient

Petrolatum 33%

Purpose

Skin Protectant

Uses

- Temporarily protects minor: cuts, scrapes, and burns
- Temporarily protects and helps relieve chafed, chapped or cracked skin
- Helps prevent and protect from the drying effects of wind and cold weather

Warnings

For external use only

When using this product do not get into the eyes

Stop use and ask a doctor if

- Condition worsens
- Symptoms last more than 7 days or clear up and occur again within a few days

Do not use on

- deep or puncture wounds
- animal bites
- serious burns

Keep out of reach of children. In case of accidental ingestion contact a physician or Poison Control Center right away.

Directions

Directions apply as needed

Inactive Ingredients

Inactive Ingredients: Water, Propylene Glycol, Mineral Oil, PEG-30 Dipolyhydroxystearate, Lanolin Alcohols, Paraffin, DMDM Hydantoin, Methylparaben, Sodium Chloride, Propylparaben